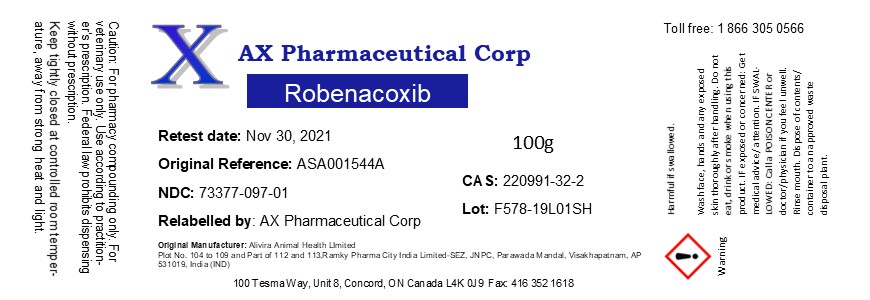 DRUG LABEL: Robenacoxib
NDC: 73377-097 | Form: POWDER
Manufacturer: AX Pharmaceutical Corp
Category: other | Type: BULK INGREDIENT
Date: 20201231

ACTIVE INGREDIENTS: ROBENACOXIB 1 g/1 g

Robenacoxib